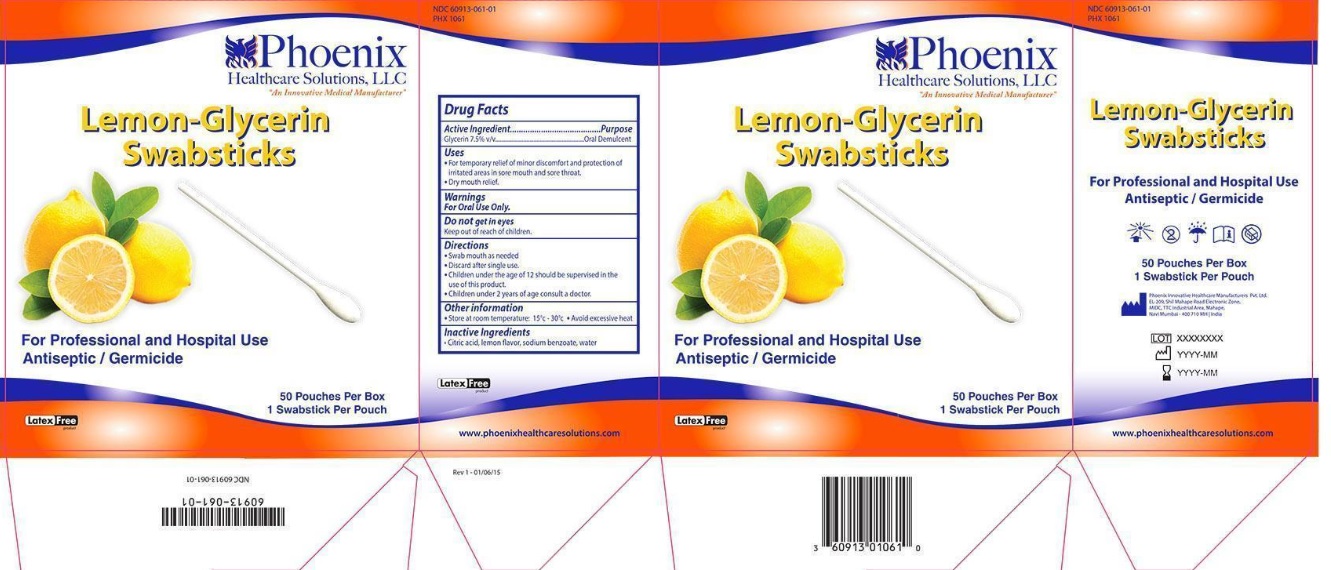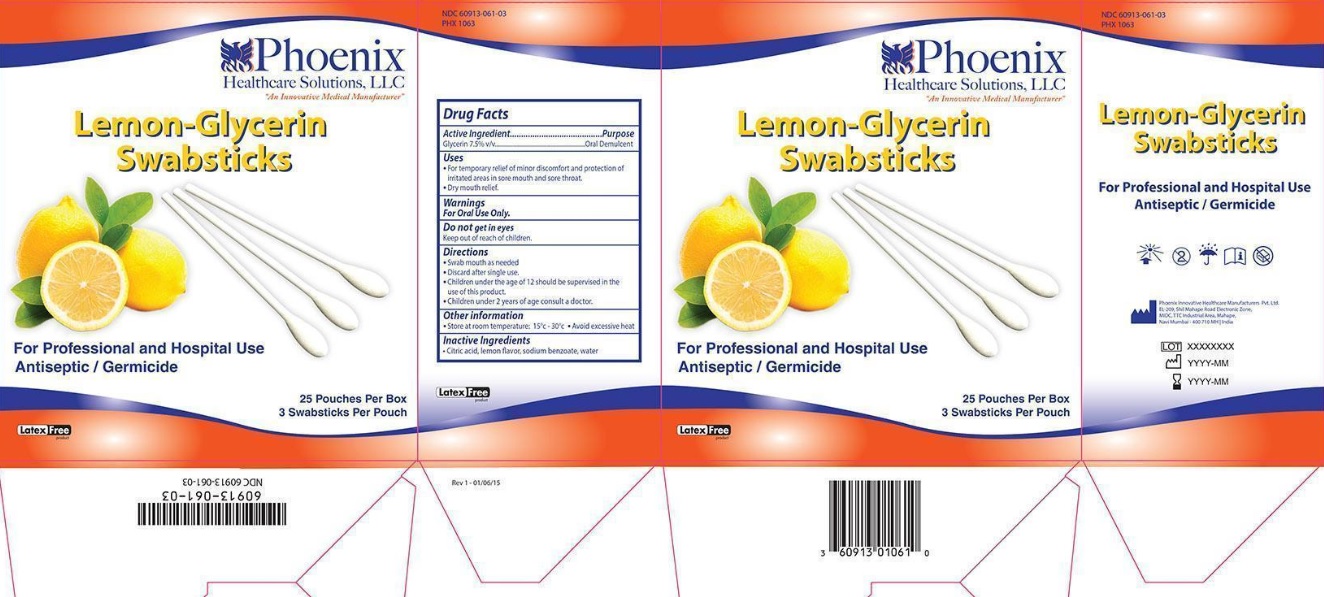 DRUG LABEL: Lemon Glycerine
NDC: 60913-061 | Form: SWAB
Manufacturer: PHOENIX HEALTHCARE SOLUTIONS, LLC
Category: otc | Type: HUMAN OTC DRUG LABEL
Date: 20251023

ACTIVE INGREDIENTS: GLYCERIN 7.5 g/100 g
INACTIVE INGREDIENTS: SODIUM BENZOATE; CITRIC ACID MONOHYDRATE; WATER

Granex Lemon Glycerine Swabstick

Active Ingredient

Glycerin 7.5% v/v

Purpose

Oral Demulcent

Uses

- For temporary relief of minor discomfort and protection of irritated areas in sore mouth and sore throat.
- Dry mouth relief.

Warnings

For Oral Use Only.

Do not use

Do not get in eyes

Keep out of reach of children

Directions:

- Swab mouth as needed
- Discard after single use.
- Children under the age of 12 should be supervised in the use of this product.
- Children under 2 years of age consult a doctor.

Other information

- Store at room temperature: 15 C - 30 C
- Avoid excessive heat

Inactive ingredients:

Citric acid, lemon flavor, sodium benzoate, water

Principal Display Panel

NDC 60913-061-01

Phoenix Healthcare Solutions LLC

"An Innovative Medical Manufacturer"

Lemon-Glycerine Swabsticks

For Professional and Hospital Use

Antiseptic/Germicide

50 Pouches Per Box

1 Swabstick Per Pouch

NDC 60913-061-03

Phoenix Healthcare Solutions LLC

"An Innovative Medical Manufacturer"

Lemon-Glycerine Swabsticks

For Professional and Hospital Use

Antiseptic/Germicide

25 Pouches Per Box

3 Swabstick Per Pouch